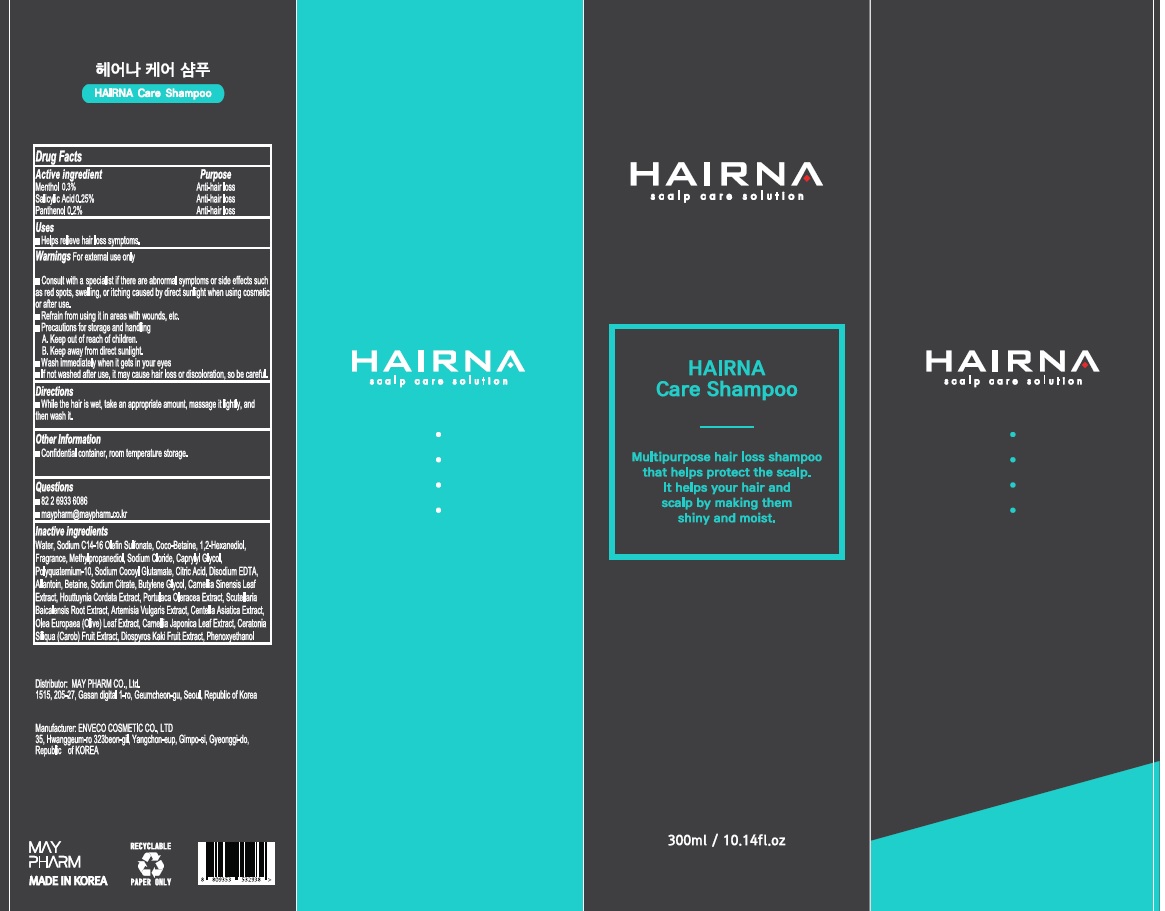 DRUG LABEL: HAIRNA Care
NDC: 82344-060 | Form: SHAMPOO
Manufacturer: MAYPHARM
Category: otc | Type: HUMAN OTC DRUG LABEL
Date: 20211129

ACTIVE INGREDIENTS: Menthol 0.3 g/100 mL; Salicylic Acid 0.25 g/100 mL; Panthenol 0.20 g/100 mL
INACTIVE INGREDIENTS: Water; Sodium C14-16 Olefin Sulfonate

ACTIVE INGREDIENTS

Menthol 0.3%
Salicylic Acid 0.25%
Panthenol 0.20%

PURPOSE

Anti-hair loss

Uses

■ Helps relieve hair loss symptoms.

WARNINGS

For external use only

■ Consult with a specialist if there are abnormal symptoms or side effects such as red spots, swelling, or itching caused by direct sunlight when using cosmetics or after use.
■ Refrain from using it in areas with wounds, etc.
■ Precautions for storage and handling
A. Keep out of reach of children.
B. Keep away from direct sunlight.
■ Wash immediately when it gets in your eyes
■ If not washed after use, it may cause hair loss or discoloration, so be careful.

KEEP OUT OF REACH OF CHILDREN

Directions

■ While the hair is wet, take an appropriate amount, massage it lightly, and then wash it.

Other Information

■ Confidential container, room temperature storage.

Questions

■ 82 2 6933 6086
■ maypharm@maypharm.co.kr

INACTIVE INGREDIENTS

Water, Sodium C14-16 Olefin Sulfonate, Coco-Betaine, 1,2-Hexanediol, Fragrance, Methylpropanediol, Sodium Cloride, Caprylyl Glycol, Polyquaternium-10, Sodium Cocoyl Glutamate, Citric Acid, Disodium EDTA, Allantoin, Betaine, Sodium Citrate, Butylene Glycol, Camellia Sinensis Leaf Extract, Houttuynia Cordata Extract, Portulaca Oleracea Extract, Scutellaria Baicalensis Root Extract, Artemisia Vulgaris Extract, Centella Asiatica Extract, Olea Europaea (Olive) Leaf Extract, Camellia Japonica Leaf Extract, Ceratonia Siliqua (Carob) Fruit Extract, Diospyros Kaki Fruit Extract, Phenoxyethanol